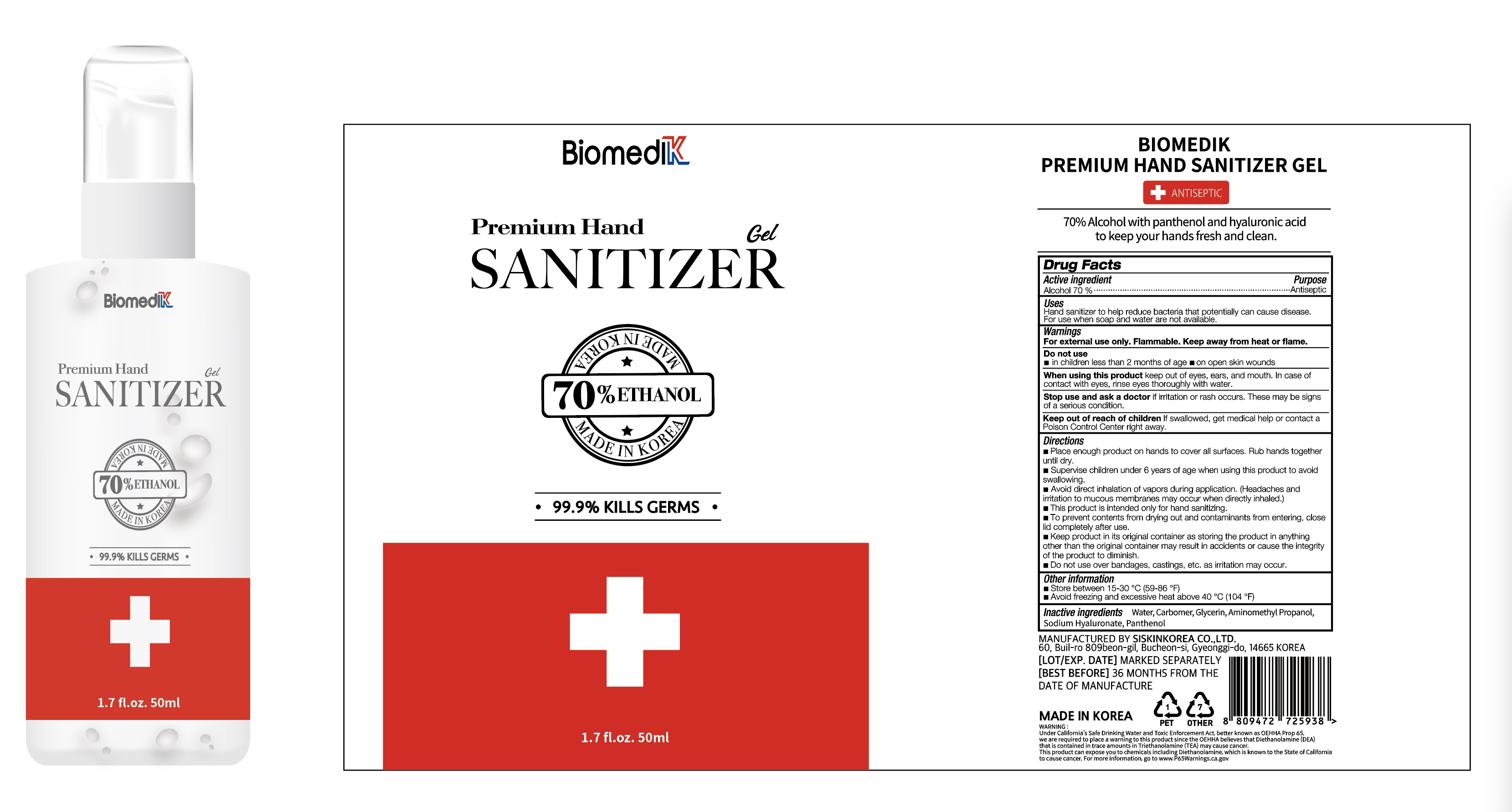 DRUG LABEL: BIOMEDIK Premium Hand Sanitizer Gel
NDC: 74514-7005 | Form: GEL
Manufacturer: SISKINKOREA CO.,LTD.
Category: otc | Type: HUMAN OTC DRUG LABEL
Date: 20200614

ACTIVE INGREDIENTS: ALCOHOL 35 mL/50 mL
INACTIVE INGREDIENTS: GLYCERIN; AMINOMETHYLPROPANOL; PANTHENOL; WATER; HYALURONATE SODIUM; CARBOMER HOMOPOLYMER, UNSPECIFIED TYPE

BIOMEDIK Premium Hand Sanitizer Gel [74514-7005-1] 50 mL, Bottle+Pump